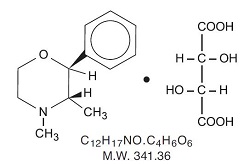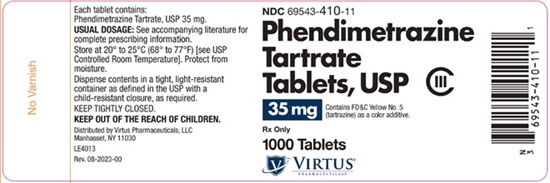 DRUG LABEL: PHENDIMETRAZINE TARTRATE
NDC: 69543-410 | Form: TABLET
Manufacturer: Virtus Pharmaceuticals, LLC
Category: prescription | Type: HUMAN PRESCRIPTION DRUG LABEL
Date: 20251219
DEA Schedule: CIII

ACTIVE INGREDIENTS: PHENDIMETRAZINE TARTRATE 35 mg/1 1
INACTIVE INGREDIENTS: STARCH, CORN; FD&C YELLOW NO. 5; LACTOSE MONOHYDRATE; POVIDONE, UNSPECIFIED; SILICON DIOXIDE; STEARIC ACID; SUCROSE

Phendimetrazine Tartrate Tablets USP, 35 mg CIII
Rx only

DESCRIPTION

Phendimetrazine tartrate, as the dextro isomer, has the chemical name of (2s,3s,)-3,4-dimethyl-2-phenylmorpholine L-(+)-tartrate (1:1).

The structural formula is as follows:

Phendimetrazine tartrate is a white, odorless crystalline powder. It is freely soluble in water; sparingly soluble in warm alcohol; insoluble in chloroform, acetone, ether and benzene.

Each tablet, for oral administration, contains 35 mg of phendimetrazine tartrate.

Inactive Ingredients: confectioner’s sugar (sucrose and corn starch), lactose monohydrate, povidone, pregelatinized starch, silicon dioxide and stearic acid. The yellow tablets also contain: FD&C yellow No. 5 (see PRECAUTIONS).

CLINICAL PHARMACOLOGY

Phendimetrazine tartrate is a phenylalkylamine sympathomimetic amine with pharmacological activity similar to the prototype drugs of this class used in obesity, the amphetamines. Actions include central nervous system stimulation and elevation of blood pressure. Tachyphylaxis and tolerance have been demonstrated with all drugs of this class in which these phenomena have been looked for.

Drugs of this class used in obesity are commonly known as “anorectics” or “anorexigenics”. It has not been established, however, that the action of such drugs in treating obesity is primarily one of appetite suppression. Other central nervous system actions or metabolic effects, may be involved, for example.

Adult obese subjects instructed in dietary management and treated with “anorectic” drugs lose more weight on the average than those treated with placebo and diet, as determined in relatively short term clinical trials.

The magnitude of increased weight loss of drug-treated patients over placebo-treated patients is only a fraction of a pound a week. The rate of weight loss is greatest in the first weeks of therapy for both drug and placebo subjects and tends to decrease in succeeding weeks. The possible origins of the increased weight loss due to the various drug effects are not established. The amount of weight loss associated with the use of an anorectic drug varies from trial to trial and the increased weight loss appears to be related in part to variables other than the drug prescribed, such as the physician investigator, the population treated and the diet prescribed. Studies do not permit conclusions as to the relative importance of the drug and non-drug factors on weight loss.

The natural history of obesity is measured in years, whereas the studies cited are restricted to a few weeks duration, thus, the total impact of drug-induced weight loss over that of diet alone must be considered clinically limited.

INDICATIONS AND USAGE

Phendimetrazine tartrate tablets are indicated in the management of exogenous obesity as a short term adjunct (a few weeks) in a regimen of weight reduction based on caloric restriction. The limited usefulness of agents of this class (see CLINICAL PHARMACOLOGY) should be measured against possible risk factors inherent in their use such as those described below.

CONTRAINDICATIONS

Known hypersensitivity or idiosyncratic reactions to sympathomimetics.

Advanced arteriosclerosis, symptomatic cardiovascular disease, moderate and severe hypertension, hyperthyroidism and glaucoma.

Highly nervous or agitated patients.

Patients with a history of drug abuse.

Patients taking other CNS stimulants, including monoamine oxidase inhibitors.

WARNINGS

Tolerance to the anorectic effect of phendimetrazine develops within a few weeks. When this occurs, its use should be discontinued; the maximum recommended dose should not be exceeded.

Use of phendimetrazine tartrate within 14 days following the administration of monoamine oxidase inhibitors may result in a hypertensive crisis.

Abrupt cessation of administration following prolonged high dosage results in extreme fatigue and depression. Because of the effect on the central nervous system, phendimetrazine may impair the ability of the patient to engage in potentially hazardous activities such as operating machinery or driving a motor vehicle; the patient should therefore be cautioned accordingly.

PRECAUTIONS

Caution is to be exercised in prescribing phendimetrazine tartrate for patients with even mild hypertension.

Insulin requirements in diabetes mellitus may be altered in association with the use of phendimetrazine and the concomitant dietary regimen.

Phendimetrazine may decrease the hypotensive effect of guanethidine.

The least amount feasible should be prescribed or dispensed at one time in order to minimize the possibility of overdosage.

The phendimetrazine tartrate yellow tablets contain FD&C yellow No. 5 (tartrazine) which may cause allergic type reactions (including bronchial asthma) in certain susceptible individuals. Although the overall incidence of FD&C yellow No. 5 (tartrazine) sensitivity in the general population is low, it is frequently seen in patients who also have aspirin hypersensitivity.

Usage in Pregnancy

Safe use in pregnancy has not been established. Until more information is available, phendimetrazine tartrate should not be taken by women who are or who may become pregnant unless, in the opinion of the physician, the potential benefits outweigh the possible hazards.

Usage in Children

Phendimetrazine tartrate is not recommended for use in children under 12 years of age.

ADVERSE REACTIONS

Cardiovascular: Palpitation, tachycardia, elevated blood pressure.

Central Nervous System: Overstimulation, restlessness, insomnia, agitation, flushing, tremor, sweating, dizziness, headache, psychotic state, blurring of vision.

Gastrointestinal: Dryness of the mouth, nausea, diarrhea, constipation, stomach pain.

Genitourinary: Urinary frequency, dysuria, changes in libido.

DRUG ABUSE AND DEPENDENCE

Controlled Substance

Phendimetrazine tartrate tablets are defined by the Drug Enforcement Administration as a Schedule III controlled substance.

Dependence

Phendimetrazine tartrate is related chemically and pharmacologically to the amphetamines. Amphetamines and related stimulant drugs have been extensively abused and the possibility of abuse of phendimetrazine should be kept in mind when evaluating the desirability of including a drug as part of a weight reduction program. Abuse of amphetamines and related drugs may be associated with intense psychological dependence and severe social dysfunction. There are reports of patients who have increased the dosage to many times that recommended. Abrupt cessation following prolonged high dosage administration results in extreme fatigue and mental depression; changes are also noted on the sleep EEG. Manifestations of chronic intoxication with anorectic drugs include severe dermatoses, marked insomnia, irritability, hyperactivity and personality changes. The most severe manifestation of chronic intoxications is psychosis, often clinically indistinguishable from schizophrenia.

OVERDOSAGE

Acute overdosage with phendimetrazine tartrate may manifest itself by the following signs and symptoms: unusual restlessness, confusion, belligerence, hallucinations and panic states. Fatigue and depression usually follow the central stimulation. Cardiovascular effects include arrhythmias, hypertension or hypotension and circulatory collapse. Gastrointestinal symptoms include nausea, vomiting, diarrhea and abdominal cramps. Poisoning may result in convulsions, coma and death.

The management of overdosage is largely symptomatic. It includes sedation with a barbiturate. If hypertension is marked, the use of a nitrate or rapid-acting alpha receptor-blocking agent should be considered. Experience with hemodialysis or peritoneal dialysis is inadequate to permit recommendations for its use.

DOSAGE AND ADMINISTRATION

Usual Adult Dose: 1 tablet (35 mg) b.i.d. or t.i.d., one hour before meals.

Dosage should be individualized to obtain an adequate response with the lowest effective dosage. In some cases 1/2 tablet (17.5 mg) per dose may be adequate. Dosage should not exceed 2 tablets t.i.d.

HOW SUPPLIED

Phendimetrazine Tartrate Tablet 35 mg is a yellow, bisected, round tablet; imprinted “E 76”.

NDC 69543-410-10 bottles of 100 tablets
NDC 69543-410-11 bottles of 1000 tablets

Storage

Store at 20° to 25°C (68° to 77°F) [see USP Controlled Room Temperature]. Protect from moisture.

Dispense in a tight, light-resistant, container as defined in the USP, with a child-resistant closure (as required).

To report SUSPECTED ADVERSE REACTIONS, contact Virtus Pharmaceuticals, LLC at 1-888-848-3593 or FDA at 1-800-FDA-1088 or www.fda.gov/medwatch.

Distributed by
Virtus Pharmaceuticals, LLC
Langhorne, PA 19047

Rev. 08/2023

MF4055REV08/23
OE2826

PACKAGE/LABEL PRINCIPAL DISPLAY PANEL

Phendimetrazine Tartrate Tablets, USP 35 mg, 1000s Label Text

NDC 69543-410-11

Phendimetrazine
Tartrate
Tablets, USP CIII

35 mg

Contains FD&C Yellow No. 5
(tartrazine) as a color additive.

Rx Only

1000 Tablets

VIRTUS®
Pharmaceuticals